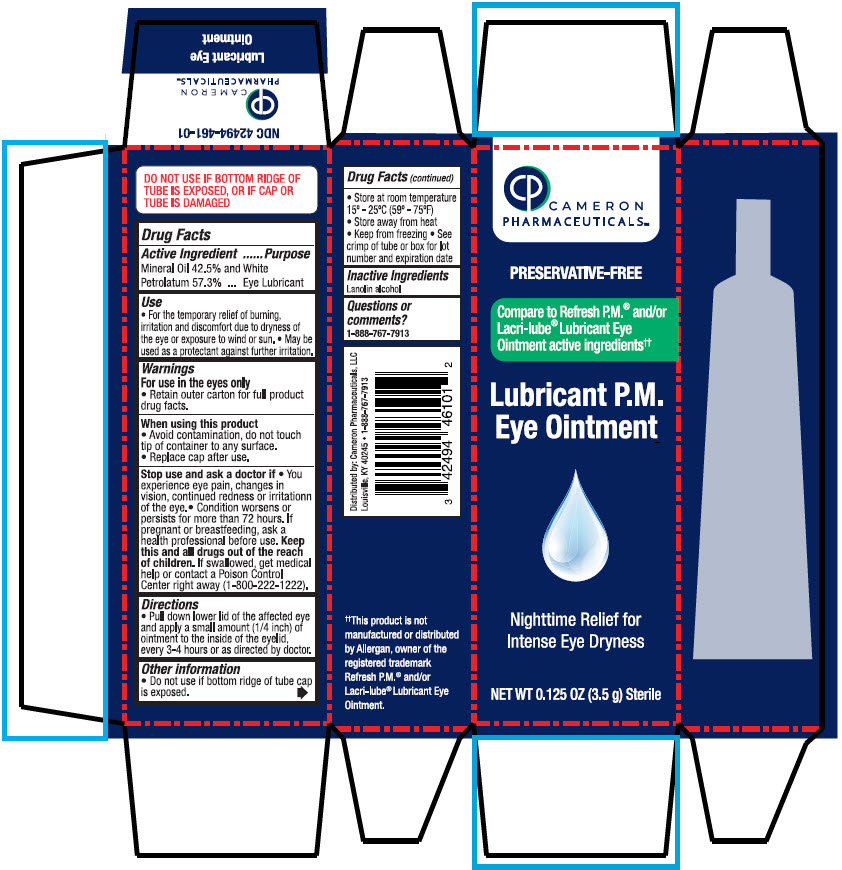 DRUG LABEL: Lubricant PM Eye
NDC: 42494-461 | Form: SOLUTION/ DROPS
Manufacturer: Cameron Pharmaceuticals
Category: otc | Type: HUMAN OTC DRUG LABEL
Date: 20241113

ACTIVE INGREDIENTS: MINERAL oil 425 mg/1 g; PETROLATUM 568 mg/1 g
INACTIVE INGREDIENTS: LANOLIN ALCOHOLS

Lubricant PM Eye Ointment

Drug Facts

Active Ingredient

Mineral Oil 42.5% and White Petrolatum 57.3%

Purpose

Eye Lubricant

Use

- For the temporary relief of burning, irritation and discomfort due to dryness of the eye or exposure to wind or sun.
- May be used as a protectant against further irritation.

Warnings

For use in the eyes only

- Retain outer carton for full product drug facts.

When using this product

- Avoid contamination, do not touch tip of container to any surface.
- Replace cap after use.

Stop use and ask a doctor if

- You experience eye pain, changes in vision, continued redness or irritationn of the eye.
- Condition worsens or persists for more than 72 hours.

PREGNANCY OR BREAST FEEDING

If pregnant or breastfeeding, ask a health professional before use.

KEEP OUT OF REACH OF CHILDREN

Keep this and all drugs out of the reach of children. If swallowed, get medical help or contact a Poison Control Center right away (1-800-222-1222).

Directions

- Pull down lower lid of the affected eye and apply a small amount (1/4 inch) of ointment to the inside of the eyelid, every 3-4 hours or as directed by doctor.

Other information

- Do not use if bottom ridge of tube cap is exposed.
- Store at room temperature 15° - 25°C (59° - 75°F)
- Store away from heat
- Keep from freezing
- See crimp of tube or box for lot number and expiration date

Inactive Ingredients

Lanolin alcohol

Questions or comments?

1-888-767-7913

Distributed by: Cameron Pharmaceuticals, LLC
Louisville, KY 40245

PRINCIPAL DISPLAY PANEL - 3.5 g Bottle Carton

CAMERON
PHARMACEUTICALS™

PRESERVATIVE-FREE

Compare to Refresh P.M.® and/or
Lacri-lube® Lubricant Eye
Ointment active ingredients††

Lubricant P.M.
Eye Ointment

Nighttime Relief for
Intense Eye Dryness

NET WT 0.125 OZ (3.5 g) Sterile